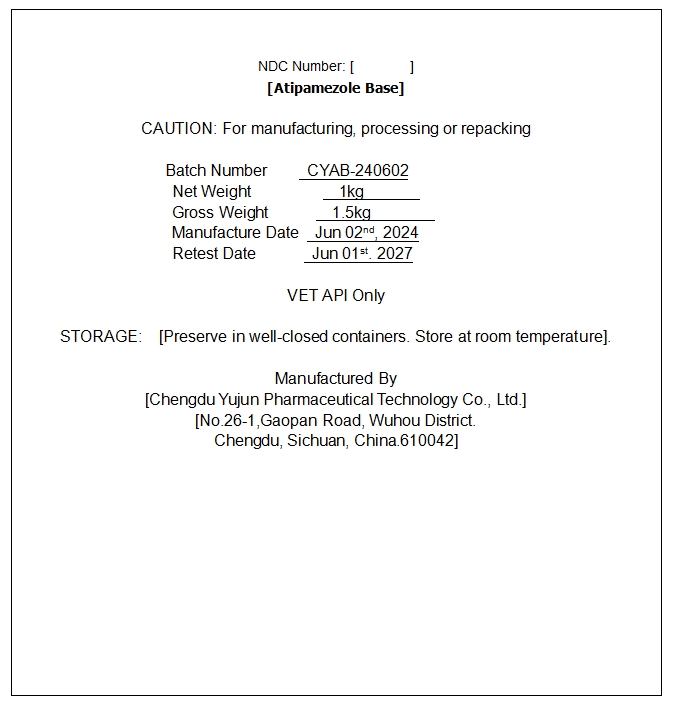 DRUG LABEL: Atipamezole Base
NDC: 86230-116 | Form: POWDER
Manufacturer: Chengdu Yujun Pharmaceutical Technology Co., Ltd
Category: other | Type: BULK INGREDIENT - ANIMAL DRUG
Date: 20250721

ACTIVE INGREDIENTS: Atipamezole 1 kg/1 kg

Atipamezole Base

Atipamezole Base

Add image transcription here...